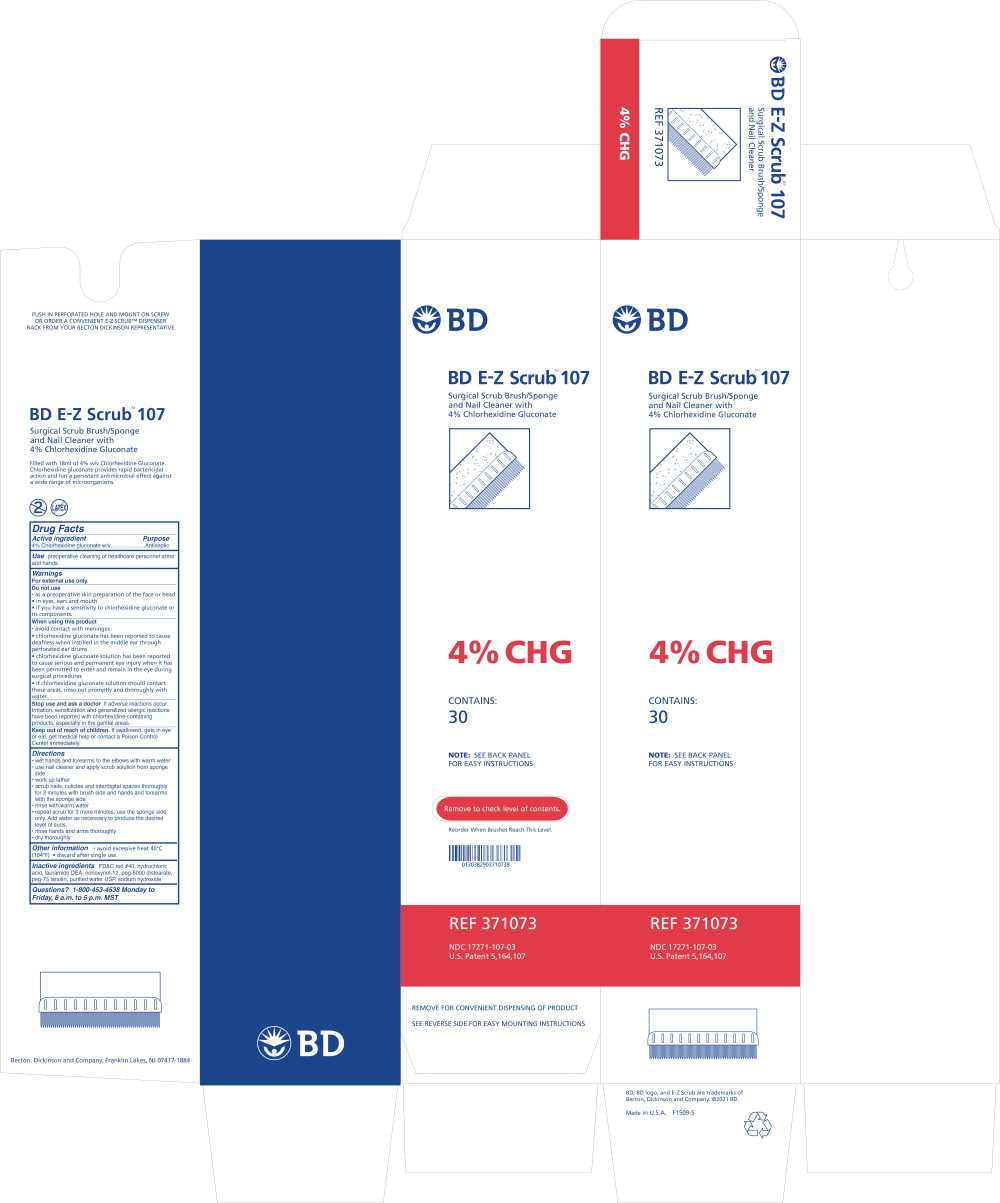 DRUG LABEL: BD E-Z Scrub 107
NDC: 17271-107 | Form: SOLUTION
Manufacturer: Becton Dickinson and Company
Category: otc | Type: HUMAN OTC DRUG LABEL
Date: 20251208

ACTIVE INGREDIENTS: CHLORHEXIDINE GLUCONATE
 40 g/1000 mL
INACTIVE INGREDIENTS: FD&C RED NO. 40; HYDROCHLORIC ACID; LAURIC DIETHANOLAMIDE; NONOXYNOL-12; PEG-150 DISTEARATE; PEG-75 LANOLIN; WATER; SODIUM HYDROXIDE

Drug Facts

Active ingredient

4% Chlorhexidine gluconate w/v

Purpose

Antiseptic

Use

preoperative cleaning of healthcare personnel arms and hands.

Warnings

For external use only.

Do not use

- as a preoperative skin preparation of the face or head
- in eyes, ears and mouth
- if you have a sensitivity to chlorhexidine gluconate or its components.

When using this product

- avoid contact with meninges
- chlorhexidine gluconate has been reported to cause deafness when instilled in the middle ear through perforated ear drums
- chlorhexidine gluconate solution has been reported to cause serious and permanent eye injury when it has been permitted to enter and remain in the eye during surgical procedures
- if chlorhexidine gluconate solution should contact these areas, rinse out promptly and thoroughly with water.

Stop use and ask a doctor if adverse reactions occur. Irritation, sensitization and generalized allergic reactions have been reported with chlorhexidine-containing products, especially in the genital areas.

Keep out of reach of children. If swallowed, gets in eye or ear, get medical help or contact a Poison Control Center immediately.

Directions

- wet hands and forearms to the elbows with warm water
- use nail cleaner and apply scrub solution from sponge side
- work up lather
- scrub nails, cuticles and interdigital spaces thoroughly for 3 minutes with brush side and hands and forearms with the sponge side
- rinse with warm water
- repeat scrub for 3 more minutes, use the sponge side only. Add water as necessary to produce the desired level of suds.
- rinse hands and arms thoroughly
- dry thoroughly

Other information

- avoid excessive heat 40°C (104°F)
- discard after single use.

Inactive ingredients

FD&C red #40, hydrochloric acid, lauramide DEA, nonoxynol-12, peg-6000 distearate, peg-75 lanolin, purified water USP, sodium hydroxide

Questions?

1-800-453-4538 Monday to Friday, 8 a.m. to 5 p.m. MST

Principal Display Panel – Carton Label

BD
BD E-Z Scrub™ 107
Surgical Scrub Brush/Sponge
and Nail Cleaner with
4% Chlorhexidine Gluconate

4% CHG
CONTAINS:
30

NOTE: SEE BACK PANEL
FOR EASY INSTRUCTIONS

REF 371073
NDC 17271-107-03
U.S. Patent 5, 164, 107